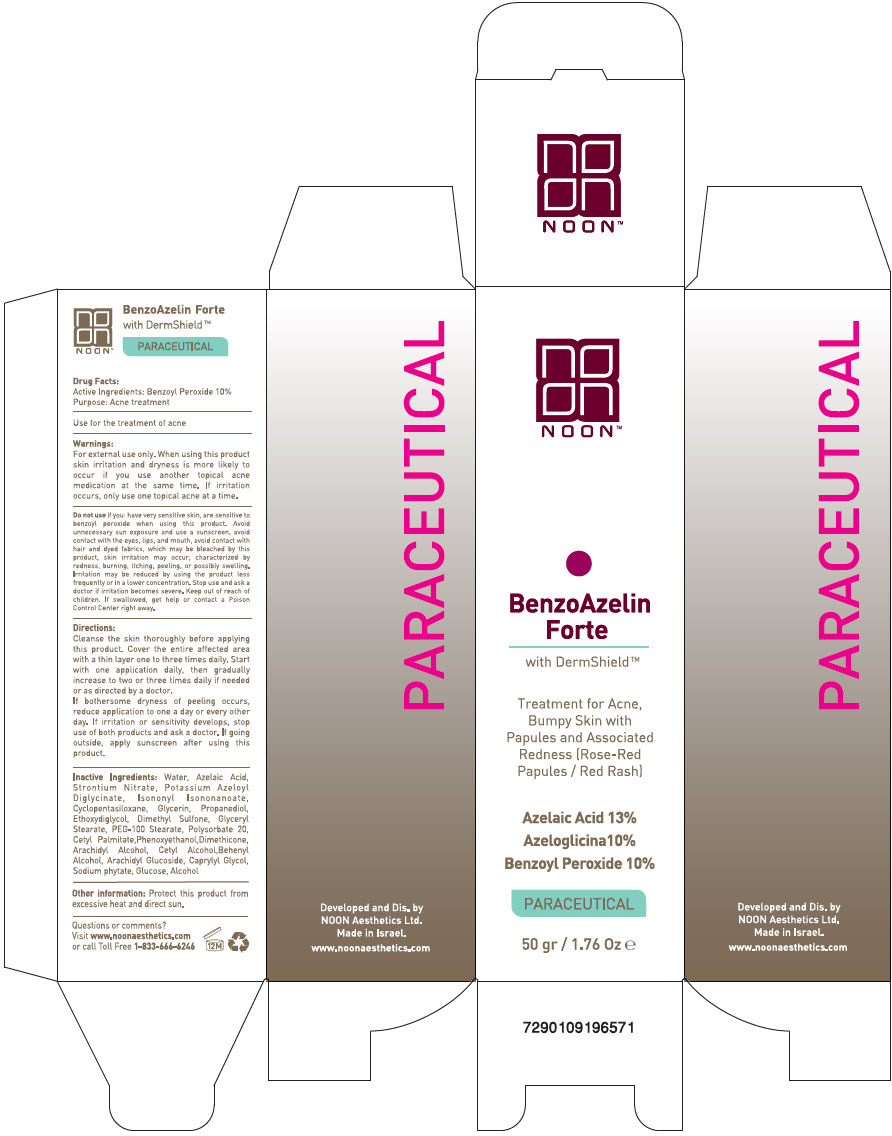 DRUG LABEL: Benzoazeline Forte
NDC: 78863-1180 | Form: CREAM
Manufacturer: Noon Aesthetics M.R. Ltd
Category: otc | Type: HUMAN OTC DRUG LABEL
Date: 20260115

ACTIVE INGREDIENTS: Benzoyl Peroxide 0.2 g/50 g
INACTIVE INGREDIENTS: Azelaic Acid; Water; Strontium Nitrate; Potassium Azeloyl Diglycinate; Isononyl Isononanoate; CYCLOMETHICONE 5; Glycerin; Propanediol; DIETHYLENE GLYCOL MONOETHYL ETHER; DIMETHYL SULFONE; GLYCERYL MONOSTEARATE; PEG-100 MONOSTEARATE; Polysorbate 20; CETYL PALMITATE; Phenoxyethanol; DIMETHICONE, UNSPECIFIED; Arachidyl Alcohol; Cetyl Alcohol; DOCOSANOL; Arachidyl Glucoside; Caprylyl Glycol; PHYTATE SODIUM; ANHYDROUS DEXTROSE; ALCOHOL

Benzoazeline Forte

Drug Facts

Active Ingredients

Benzoyl Peroxide 10%

Purpose

Acne treatment

INDICATIONS AND USAGE

Use for the treatment of acne

Warnings

For external use only.

When using this product skin irritation and dryness is more likely to occur if you use another topical acne medication at the same time. If irritation occurs, only use one topical acne at a time.

Do not use if you: have very sensitive skin, are sensitive to benzoyl peroxide when using this product. Avoid unnecessary sun exposure and use a sunscreen, avoid contact with the eyes, lips, and mouth, avoid contact with hair and dyed fabrics, which may be bleached by this product, skin irritation may occur, characterized by redness, burning, itching, peeling, or possibly swelling. Irritation may be reduced by using the product less frequently or in a lower concentration. Stop use and ask a doctor if irritation becomes severe.

Keep out of reach of children. If swallowed, get help or contact a Poison Control Center right away.

Directions

Cleanse the skin thoroughly before applying this product. Cover the entire affected area with a thin layer one to three times daily. Start with one application daily, then gradually increase to two or three times daily if needed or as directed by a doctor.

If bothersome dryness of peeling occurs, reduce application to one a day or every other day. If irritation or sensitivity develops, stop use of both products and ask a doctor.

If going outside, apply sunscreen after using this product.

Inactive Ingredients

Water, Azelaic Acid, Strontium Nitrate, Potassium Azeloyl Diglycinate, Isononyl Isononanoate, Cyclopentasiloxane, Glycerin, Propanediol, Ethoxydiglycol, Dimethyl Sulfone, Glyceryl Stearate, PEG-100 Stearate, Polysorbate 20, Cetyl Palmitate, Phenoxyethanol, Dimethicone, Arachidyl Alcohol, Cetyl Alcohol, Behenyl Alcohol, Arachidyl Glucoside, Caprylyl Glycol, Sodium phytate, Glucose, Alcohol

Other information

Protect this product form excessive heat and direct sun.

Questions or comments?

Visit www.noonaesthetics.com
Or call Toll Free 1-833-666-6246

PRINCIPAL DISPLAY PANEL - 50 gr Tube Carton

NOON ™

BenzoAzelin
Forte
with DermShield ™

Treatment for Acne,
Bumpy Skin with
Papules and Associated
Redness (Rose-Red
Papules / Red Rash)

Azelaic Acid 13%
Azeloglicina 10%
Benzoyl Peroxide 10%

PARACEUTICAL

50 gr / 1.76 Oz e